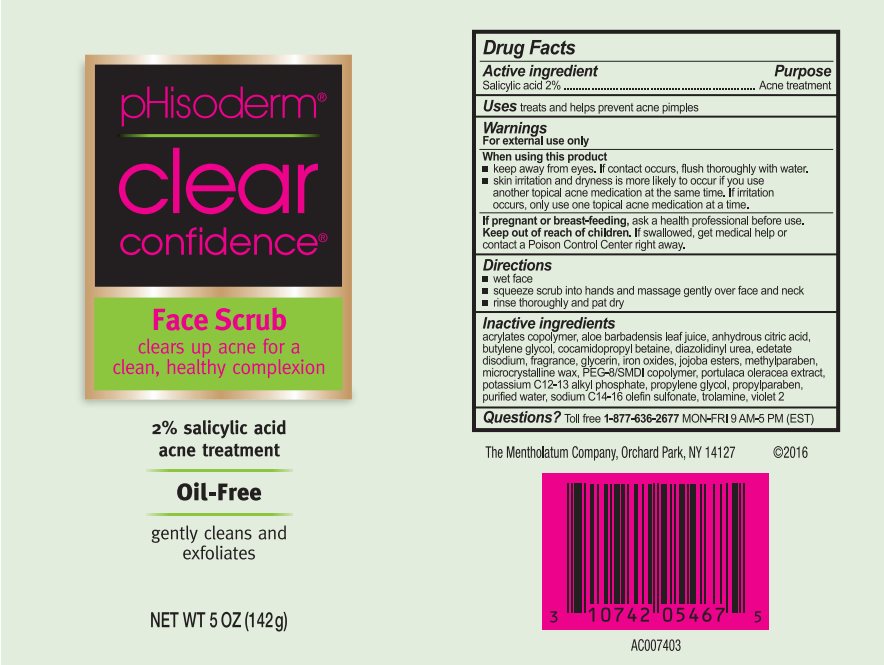 DRUG LABEL: pHisoderm Clear Confidence Face Scrub
NDC: 10742-1233 | Form: GEL
Manufacturer: The Mentholatum Company
Category: otc | Type: HUMAN OTC DRUG LABEL
Date: 20241213

ACTIVE INGREDIENTS: SALICYLIC ACID 20 mg/1 g
INACTIVE INGREDIENTS: ALOE VERA LEAF; ANHYDROUS CITRIC ACID; BUTYLENE GLYCOL; COCAMIDOPROPYL BETAINE; D&C VIOLET NO. 2; DIAZOLIDINYL UREA; EDETATE DISODIUM; FERRIC OXIDE RED; GLYCERIN; HYDROGENATED JOJOBA OIL/JOJOBA OIL, RANDOMIZED (IODINE VALUE 40-44); METHYLPARABEN; MICROCRYSTALLINE WAX; PEG-8/SMDI COPOLYMER; PURSLANE; PROPYLENE GLYCOL; PROPYLPARABEN; WATER; SODIUM C14-16 OLEFIN SULFONATE; TROLAMINE

Drug Facts - pHisoderm Clear Confidence Face Scrub

Active ingredient

Salicylic acid 2%

Purpose

Acne treatment

Uses

treats and helps prevent acne pimples

Warnings

For external use only

When using this product

- keep away from eyes. If contact occurs, flush thoroughly with water.
- skin irritation and dryness is more likely to occur if you use another topical acne medication at the same time. If irritation occurs, only use one topical acne medication at a time.

If pregnant or breast-feeding,

ask a health professional before use.

Keep out of reach of children.

If swallowed, get medical help or contact a Poison Control Center right away.

Directions

- wet face
- squeeze scrub into hands and massage gently over face and neck
- rinse thoroughly and pat dry

Inactive ingredients

acrylates copolymer, aloe barbadensis leaf juice, anhydrous citric acid, butylene glycol, cocamidopropyl betaine, diazolidinyl urea, edetate disodium, fragrance, glycerin, iron oxides, jojoba esters, methylparaben, microcrystalline wax, PEG-8/SMDI copolymer, portulaca oleracea extract, potassium C12-13 alkyl phosphate, propylene glycol, propylparaben, purified water, sodium C14-16 olefin sulfonate, trolamine, violet 2

Questions?

Toll free 1-877-636-2677 MON-FRI 9 AM-5 PM (EST)